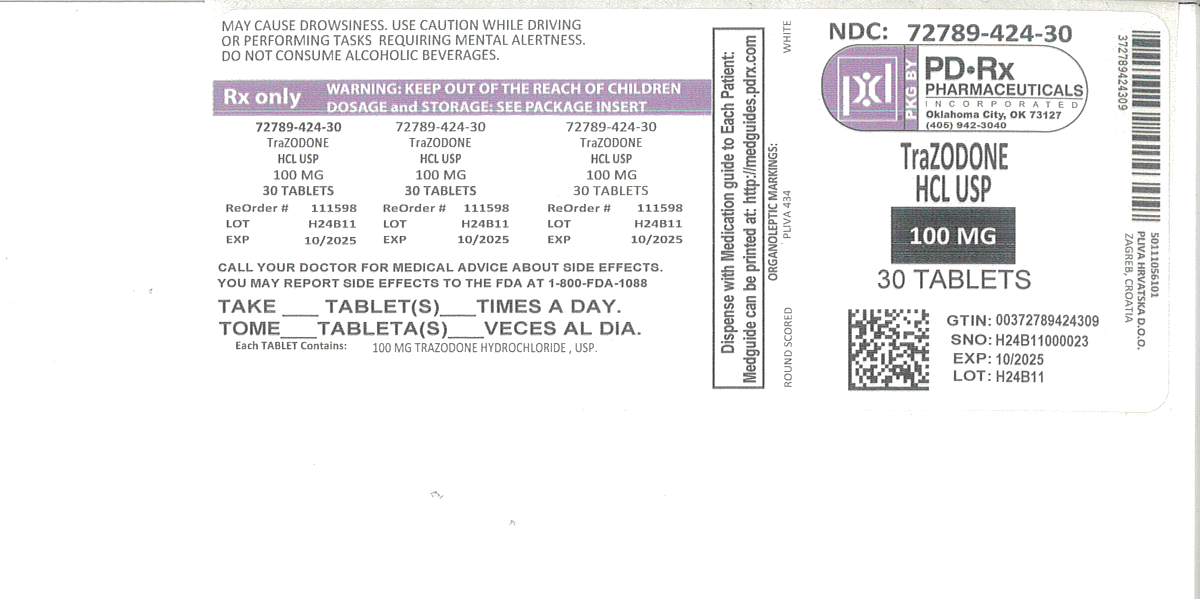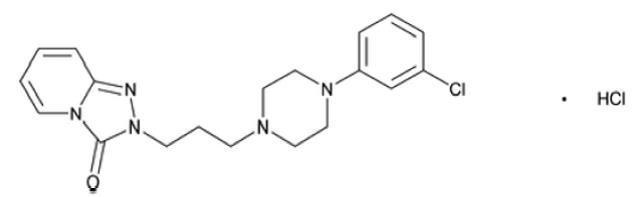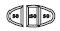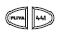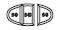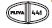 DRUG LABEL: Trazodone Hydrochloride
NDC: 72789-424 | Form: TABLET
Manufacturer: PD-Rx Pharmaceuticals, Inc.
Category: prescription | Type: HUMAN PRESCRIPTION DRUG LABEL
Date: 20260226

ACTIVE INGREDIENTS: TRAZODONE HYDROCHLORIDE 100 mg/1 1
INACTIVE INGREDIENTS: SILICON DIOXIDE; ANHYDROUS LACTOSE; MAGNESIUM STEARATE; MICROCRYSTALLINE CELLULOSE; SODIUM STARCH GLYCOLATE TYPE A POTATO

HIGHLIGHTS OF PRESCRIBING INFORMATION

These highlights do not include all the information needed to use TRAZODONE HYDROCHLORIDE TABLETS safely and effectively. See full prescribing information for TRAZODONE HYDROCHLORIDE TABLETS.
TRAZODONE HYDROCHLORIDE tablets, for oral use
Initial U.S. Approval: 1981

WARNING: SUICIDAL THOUGHTS AND BEHAVIORS

See full prescribing information for complete boxed warning.

- Antidepressants increased the risk of suicidal thoughts and behaviors in pediatric and young adult patients (5.1)

- Closely monitor for clinical worsening and emergence of suicidal thoughts and behaviors (5.1)

- Trazodone is not approved for use in pediatric patients (8.4)

1 INDICATIONS AND USAGE

Trazodone hydrochloride tablets are a selective serotonin reuptake inhibitor indicated for the treatment of major depressive disorder (MDD) (1).

2 DOSAGE AND ADMINISTRATION

- Starting dose: 150 mg in divided doses daily. May be increased by 50 mg per day every three to four days. Maximum dose: 400 mg per day in divided doses (2).
- Trazodone hydrochloride tablets should be taken shortly after a meal or light snack (2).
- Tablets should be swallowed whole or broken in half along the score line, and should not be chewed or crushed (2).
- When discontinued, gradual dose reduction is recommended (2).

3 DOSAGE FORMS AND STRENGTHS

- Scored tablets of 50 mg, 100 mg and 150 mg (3).

4 CONTRAINDICATIONS

- Concomitant use of monoamine oxidase inhibitors (MAOIs), or use within 14 days of stopping MAOIs (4).

5 WARNINGS AND PRECAUTIONS

- Serotonin Syndrome: Increased risk when co-administered with other serotonergic agents (e.g., SSRI, SNRI, triptans), but also when taken alone. If it occurs, discontinue trazodone hydrochloride tablets and initiate supportive treatment (5.2).
- Cardiac Arrhythmias: Increases the QT interval. Avoid use with drugs that also increase the QT interval and in patients with risk factors for prolonged QT interval (5.3)
- Orthostatic Hypotension and Syncope: Warn patients of risk and symptoms of hypotension (5.4).
- Increased Risk of Bleeding: Concomitant use of aspirin, nonsteroidal anti-inflammatory drugs (NSAIDs), other antiplatelet drugs, warfarin, and other anticoagulants may increase this risk (5.5).
- Priapism: Cases of painful and prolonged penile erections and priapism have been reported. Immediate medical attention should be sought if signs and symptoms of prolonged penile erections or priapism are observed (5.6).
- Activation of Mania or Hypomania: Screen for bipolar disorder and monitor for mania or hypomania (5.7).
- Potential for Cognitive and Motor Impairment: Has potential to impair judgment, thinking, and motor skills. Advise patients to use caution when operating machinery (5.9).
- Angle-Closure Glaucoma: Avoid use of antidepressants, including trazodone hydrochloride tablets, in patients with untreated anatomically narrow angles. (5.10).

6 ADVERSE REACTIONS

Most common adverse reactions (incidence ≥ 5% and twice that of placebo) are: edema, blurred vision, syncope, drowsiness, fatigue, diarrhea, nasal congestion, weight loss (6).

To report SUSPECTED ADVERSE REACTIONS, contact Teva at 1-888-838-2872 or FDA at 1-800-FDA-1088 or www.fda.gov/medwatch.

7 DRUG INTERACTIONS

- CNS Depressants: Trazodone hydrochloride tablets may enhance effects of alcohol, barbiturates, or other CNS depressants (7).

- CYP3A4 Inhibitors: Consider trazodone hydrochloride tablets dose reduction based on tolerability (2.5, 7).

- CYP3A4 Inducers: Increase in trazodone hydrochloride tablets dosage may be necessary (2.5, 7).

- Digoxin or Phenytoin: Monitor for increased digoxin or phenytoin serum levels (7).

- Warfarin: Monitor for increased or decreased prothrombin time (7).

FULL PRESCRIBING INFORMATION

WARNING: SUICIDAL THOUGHTS AND BEHAVIORS

Antidepressants increased the risk of suicidal thoughts and behaviors in pediatric and young adult patients in short-term studies. Closely monitor all antidepressant-treated patients for clinical worsening, and for emergence of suicidal thoughts and behaviors [see Warnings and Precautions (5.1)] . Trazodone hydrochloride tablets are not approved for use in pediatric patients [see Use in Specific Populations (8.4)] .

1 INDICATIONS AND USAGE

Trazodone hydrochloride tablets are indicated for the treatment of major depressive disorder (MDD) in adults.

2 DOSAGE AND ADMINISTRATION

2.1 Dose Selection

An initial dose of 150 mg/day in divided doses is suggested. The dosage should be initiated at a low-dose and increased gradually, noting the clinical response and any evidence of intolerance. Occurrence of drowsiness may require the administration of a major portion of the daily dose at bedtime or a reduction of dosage.

The dose may be increased by 50 mg/day every 3 to 4 days. The maximum dose for outpatients usually should not exceed 400 mg/day in divided doses. Inpatients (i.e., more severely depressed patients) may be given up to but not in excess of 600 mg/day in divided doses.

Once an adequate response has been achieved, dosage may be gradually reduced, with subsequent adjustment depending on therapeutic response.

2.2 Important Administration Instructions

Trazodone hydrochloride tablets can be swallowed whole or administered as a half tablet by breaking the tablet along the score line.

Trazodone hydrochloride tablets should be taken shortly after a meal or light snack.

2.3 Screen for Bipolar Disorder Prior to Starting Trazodone Hydrochloride Tablets

Prior to initiating treatment with trazodone hydrochloride tablets or another antidepressant, screen patients for a personal or family history of bipolar disorder, mania, or hypomania [see Warnings and Precautions (5.7)].

2.4 Switching to or from Monoamine Oxidase Inhibitor Antidepressant

At least 14 days must elapse between discontinuation of a monoamine oxidase inhibitor (MAOI) antidepressant and initiation of trazodone hydrochloride tablets. In addition, at least 14 days must elapse after stopping trazodone hydrochloride tablets before starting an MAOI antidepressant [see Contraindications (4), Warnings and Precautions (5.2)].

2.5 Dosage Recommendations for Concomitant Use with Strong CYP3A4 Inhibitors or Inducers

Coadministration with Strong CYP3A4 Inhibitors

Consider reducing trazodone hydrochloride tablets dose based on tolerability when trazodone hydrochloride tablets are coadministered with a strong CYP3A4 inhibitor [see Drug Interactions (7.1)].

Coadministration with Strong CYP3A4 Inducers

Consider increasing trazodone hydrochloride tablets dose based on therapeutic response when trazodone hydrochloride tablets are coadministered with a strong CYP3A4 inducer [see Drug Interactions (7.1)].

2.6 Discontinuation of Treatment with Trazodone Hydrochloride Tablets

Adverse reactions may occur upon discontinuation of trazodone hydrochloride tablets [See Warnings and Precautions (5.8)]. Gradually reduce the dosage rather than stopping trazodone hydrochloride tablets abruptly whenever possible.

3 DOSAGE FORMS AND STRENGTHS

Trazodone hydrochloride tablets, USP are available in the following strengths:

50 mg: White, round, compressed tablet, debossed “PLIVA 433” on one side and scored on the other side.

100 mg: White, round, compressed tablet, debossed “PLIVA 434” on one side and scored on the other side.

150 mg: White, oval, flat-faced, beveled edge tablet, scored and debossed as “PLIVA” bisect “441” on one side and tri-scored and debossed as “50” in each section on the other side.

4 CONTRAINDICATIONS

Trazodone hydrochloride tablets are contraindicated in:

- Patients taking, or within 14 days of stopping, monoamine oxidase inhibitors (MAOIs), including MAOIs such as linezolid or intravenous methylene blue, because of an increased risk of serotonin syndrome [see Warnings and Precautions (5.2), Drug Interactions (7.1)].

5 WARNINGS AND PRECAUTIONS

5.1 Suicidal Thoughts and Behaviors in Pediatric and Young Adult Patients

In pooled analyses of placebo-controlled trials of antidepressant drugs (SSRIs and other antidepressant classes) that included approximately 77,000 adult patients and over 4,400 pediatric patients, the incidence of suicidal thoughts and behaviors in pediatric and young adult patients was greater in antidepressant-treated patients than in placebo-treated patients. The drug-placebo differences in the number of cases of suicidal thoughts and behaviors per 1000 patients treated are provided in Table 1.

No suicides occurred in any of the pediatric studies. There were suicides in the adult studies, but the number was not sufficient to reach any conclusion about antidepressant drug effect on suicide.

Table 1: Risk Differences of the Number of Cases of Suicidal Thoughts or Behaviors in the Pooled Placebo-Controlled Trials of Antidepressants in Pediatric and Adult Patients
Age Range; (years) | Drug-Placebo Difference in Number of Patients of Suicidal; Thoughts or Behaviors per 1000 Patients Treated
 | Increases Compared to Placebo
< 18 | 14 additional patients
18 to 24 | 5 additional patients
 | Decreases Compared to Placebo
25 to 64 | 1 fewer patient
≥ 65 | 6 fewer patients

It is unknown whether the risk of suicidal thoughts and behaviors in pediatric and young adult patients extends to longer-term use, i.e., beyond four months. However, there is substantial evidence from placebo-controlled maintenance trials in adults with MDD that antidepressants delay the recurrence of depression.

Monitor all antidepressant-treated patients for clinical worsening and emergence of suicidal thoughts and behaviors, especially during the initial few months of drug therapy and at times of dosage changes. Counsel family members or caregivers of patients to monitor for changes in behavior and to alert the healthcare provider. Consider changing the therapeutic regimen, including possibly discontinuing trazodone hydrochloride tablets, in patients whose depression is persistently worse, or who are experiencing emergent suicidal thoughts or behaviors.

5.2 Serotonin Syndrome

Serotonin-norepinephrine reuptake inhibitors (SNRIs) and SSRIs, including trazodone hydrochloride tablets, can precipitate serotonin syndrome, a potentially life-threatening condition. The risk is increased with concomitant use of other serotonergic drugs (including triptans, tricyclic antidepressants, fentanyl, lithium, tramadol, tryptophan, buspirone, and St. John’s Wort) and with drugs that impair metabolism of serotonin, i.e., MAOIs [see Contraindications (4), Drug Interactions (7.1)]. Serotonin syndrome can also occur when these drugs are used alone.

Serotonin syndrome signs and symptoms may include mental status changes (e.g., agitation, hallucinations, delirium, and coma), autonomic instability (e.g., tachycardia, labile blood pressure, dizziness, diaphoresis, flushing, hyperthermia), neuromuscular symptoms (e.g., tremor, rigidity, myoclonus, hyperreflexia, incoordination), seizures, and gastrointestinal symptoms (e.g., nausea, vomiting, diarrhea).

The concomitant use of trazodone hydrochloride tablets with MAOIs is contraindicated. In addition, do not initiate trazodone hydrochloride tablets in a patient being treated with MAOIs such as linezolid or intravenous methylene blue. No reports involved the administration of methylene blue by other routes (such as oral tablets or local tissue injection). If it is necessary to initiate treatment with an MAOI such as linezolid or intravenous methylene blue in a patient taking trazodone hydrochloride tablets, discontinue trazodone hydrochloride tablets before initiating treatment with the MAOI [see Contraindications (4), Drug Interactions (7.1)].

Monitor all patients taking trazodone hydrochloride tablets for the emergence of serotonin syndrome. Discontinue treatment with trazodone hydrochloride tablets and any concomitant serotonergic agents immediately if the above symptoms occur, and initiate supportive symptomatic treatment. If concomitant use of trazodone hydrochloride tablets with other serotonergic drugs is clinically warranted, inform patients of the increased risk for serotonin syndrome and monitor for symptoms.

5.3 Cardiac Arrhythmias

Clinical studies indicate that trazodone hydrochloride may be arrhythmogenic in patients with preexisting cardiac disease. Arrhythmias identified include isolated PVCs, ventricular couplets, tachycardia with syncope, and torsade de pointes. Postmarketing events, including torsade de pointes have been reported at doses of 100 mg or less with the immediate-release form of trazodone hydrochloride. Trazodone hydrochloride should also be avoided in patients with a history of cardiac arrhythmias, as well as other circumstances that may increase the risk of the occurrence of torsade de pointes and/or sudden death, including symptomatic bradycardia, hypokalemia or hypomagnesemia, and the presence of congenital prolongation of the QT interval. Trazodone hydrochloride is not recommended for use during the initial recovery phase of myocardial infarction. Caution should be used when administering trazodone hydrochloride to patients with cardiac disease and such patients should be closely monitored, since antidepressant drugs (including trazodone hydrochloride) may cause cardiac arrhythmias [see Adverse Reactions (6.2)].

Trazodone hydrochloride prolongs the QT/QTc interval. The use of trazodone hydrochloride should be avoided in patients with known QT prolongation or in combination with other drugs that are inhibitors of CYP3A4 (e.g., itraconazole, clarithromycin, voriconazole), or known to prolong QT interval including Class 1A antiarrhythmics (e.g., quinidine, procainamide) or Class 3 antiarrhythmics (e.g., amiodarone, sotalol), certain antipsychotic medications (e.g., ziprasidone, chlorpromazine, thioridazine), and certain antibiotics (e.g., gatifloxacin). Concomitant administration of drugs may increase the risk of cardiac arrhythmia [see Drug Interactions (7.1)].

5.4 Orthostatic Hypotension and Syncope

Hypotension, including orthostatic hypotension and syncope has been reported in patients receiving trazodone hydrochloride. Concomitant use with an antihypertensive may require a reduction in the dose of the antihypertensive drug.

5.5 Increased Risk of Bleeding

Drugs that interfere with serotonin reuptake inhibition, including trazodone hydrochloride, increase the risk of bleeding events. Concomitant use of aspirin, nonsteroidal anti-inflammatory drugs (NSAIDS), other antiplatelet drugs, warfarin, and other anticoagulants may add to this risk. Case reports and epidemiological studies (case-control and cohort design) have demonstrated an association between use of drugs that interfere with serotonin reuptake and the occurrence of gastrointestinal bleeding. Bleeding events related to drugs that interfere with serotonin reuptake have ranged from ecchymosis, hematoma, epistaxis, and petechiae to life-threatening hemorrhages.

Inform patients about the risk of bleeding associated with the concomitant use of trazodone hydrochloride and antiplatelet agents or anticoagulants. For patients taking warfarin, carefully monitor coagulation indices when initiating, titrating, or discontinuing trazodone hydrochloride.

5.6 Priapism

Cases of priapism (painful erections greater than 6 hours in duration) have been reported in men receiving trazodone hydrochloride tablets. Priapism, if not treated promptly, can result in irreversible damage to the erectile tissue. Men who have an erection lasting greater than 4 hours, whether painful or not, should immediately discontinue the drug and seek emergency medical attention [see Adverse Reactions (6.2), Overdosage (10)].

Trazodone hydrochloride tablets should be used with caution in men who have conditions that might predispose them to priapism (e.g., sickle cell anemia, multiple myeloma, or leukemia), or in men with anatomical deformation of the penis (e.g., angulation, cavernosal fibrosis, or Peyronie’s disease).

5.7 Activation of Mania or Hypomania

In patients with bipolar disorder, treating a depressive episode with trazodone hydrochloride tablets or another antidepressant may precipitate a mixed/manic episode. Activation of mania/hypomania has been reported in a small proportion of patients with major affective disorder who were treated with antidepressants. Prior to initiating treatment with trazodone hydrochloride tablets, screen patients for any personal or family history of bipolar disorder, mania, or hypomania [see Dosage and Administration (2.3)].

5.8 Discontinuation Syndrome

Adverse reactions after discontinuation of serotonergic antidepressants, particularly after abrupt discontinuation, include: nausea, sweating, dysphoric mood, irritability, agitation, dizziness, sensory disturbances (e.g., paresthesia, such as electric shock sensations), tremor, anxiety, confusion, headache, lethargy, emotional lability, insomnia, hypomania, tinnitus, and seizures. A gradual reduction in dosage rather than abrupt cessation is recommended whenever possible [See Dosage and Administration (2.6)].

5.9 Potential for Cognitive and Motor Impairment

Trazodone hydrochloride tablets may cause somnolence or sedation and may impair the mental and/or physical ability required for the performance of potentially hazardous tasks. Patients should be cautioned about operating hazardous machinery, including automobiles, until they are reasonably certain that the drug treatment does not affect them adversely.

5.10 Angle-Closure Glaucoma

The pupillary dilation that occurs following use of many antidepressant drugs including trazodone hydrochloride tablets may trigger an angle closure attack in a patient with anatomically narrow angles who does not have a patent iridectomy. Avoid use of antidepressants, including trazodone hydrochloride tablets, in patients with untreated anatomically narrow angles.

5.11 Hyponatremia

Hyponatremia may occur as a result of treatment with SNRIs and SSRIs, including trazodone hydrochloride tablets. Cases with serum sodium lower than 110 mmol/L have been reported. Signs and symptoms of hyponatremia include headache, difficulty concentrating, memory impairment, confusion, weakness, and unsteadiness, which can lead to falls. Signs and symptoms associated with more severe and/or acute cases have included hallucination, syncope, seizure, coma, respiratory arrest, and death. In many cases, this hyponatremia appears to be the result of the syndrome of inappropriate antidiuretic hormone secretion (SIADH).

In patients with symptomatic hyponatremia, discontinue trazodone hydrochloride tablets and institute appropriate medical intervention. Elderly patients, patients taking diuretics, and those who are volume-depleted may be at greater risk of developing hyponatremia with SSRIs and SNRIs [see Use in Specific Populations (8.5)].

6 ADVERSE REACTIONS

The following serious adverse reactions are described elsewhere in the labeling:

- Suicidal Thoughts and Behavior in Children, Adolescents and Young Adults [see Boxed Warning and Warnings and Precautions (5.1)]
- Serotonin Syndrome [see Warnings and Precautions (5.2)]
- Cardiac Arrythmias (see Warnings and Precautions (5.3)]
- Orthostatic Hypotension and Syncope [see Warnings and Precautions (5.4)]
- Increased Risk of Bleeding [see Warnings and Precautions (5.5)]
- Priapism [see Warnings and Precautions (5.6)]
- Activation of Mania or Hypomania [see Warnings and Precautions (5.7)]
- Discontinuation Syndrome [see Warnings and Precautions (5.8)]
- Potential for Cognitive and Motor Impairment [see Warnings and Precautions (5.9)]
- Angle-Closure Glaucoma [see Warnings and Precautions (5.10)]
- Hyponatremia [see Warnings and Precautions (5.11)]

6.1 Clinical Trials Experience

Because clinical trials are conducted under widely varying conditions, adverse reaction rates observed in the clinical trials of a drug cannot be directly compared to rates in the clinical trials of another drug and may not reflect the rates observed in practice.

Table 2: Common Adverse Reactions Occurring in ≥ 2% of Trazodone Hydrochloride Tablets-treated Patients and Greater than the Rate of Placebo-Treated Patients as Observed in Controlled Clinical Studies
 | Inpatients |  | Outpatients
 | Trazodone Hydrochloride Tablets | Placebo | Trazodone Hydrochloride Tablets | Placebo
 | N =142 | N=95 | N =157 | N=158
Allergic
 | 3% | 1% | 7% | 1%
Skin Condition/Edema
Autonomic
Blurred Vision | 6% | 4% | 15% | 4%
Constipation | 7% | 4% | 8% | 6%
Dry Mouth | 15% | 8% | 34% | 20%
Cardiovascular
Hypertension | 20% | 1% | 1% | *
Hypotension | 7% | 1% | 4% | 0
Syncope | 3% | 2% | 5% | 1%
CNS
Confusion | 5% | 0 | 6% | 8%
Decreased Concentration | 3% | 2% | 1% | 0
Disorientation | 2% | 0 | * | 0
Dizziness/Light-Headedness | 20% | 5% | 28% | 15%
Drowsiness | 24% | 6% | 41% | 20%
Fatigue | 11% | 4% | 6% | 3%
Headache | 10% | 5% | 20% | 16%
Nervousness | 15% | 11% | 6% | 8%
Gastrointestinal
Abdominal/Gastric Disorder | 4% | 4% | 6% | 4%
Diarrhea | 0 | 1% | 5% | 1%
Nausea/Vomiting | 10% | 1% | 13% | 10%
Musculoskeletal
Aches/Pains | 6% | 3% | 5% | 3%
Neurological
Incoordination | 5% | 0 | 2% | *
Tremors | 3% | 1% | 5% | 4%
Other
Eyes Red/Tired/Itching | 3% | 0 | 0 | 0
Head Full-Heavy | 3% | 0 | 0 | 0
Malaise | 3% | 0 | 0 | 0
Nasal/Sinus Congestion | 3% | 0 | 6% | 3%
Weight Gain | 1% | 0 | 5% | 2%
Weight Loss | * | 3% | 6% | 3%

Other adverse reactions occurring at an incidence of <2% with the use of trazodone hydrochloride in the controlled clinical studies: akathisia, allergic reaction, anemia, chest pain, delayed urine flow, early menses, flatulence, hallucinations/delusions, hematuria, hypersalivation, hypomania, impaired memory, impaired speech, impotence, increased appetite, increased libido, increased urinary frequency, missed periods, muscle twitches, numbness, paresthesia, retrograde ejaculation, shortness of breath, and tachycardia/palpitations. Occasional sinus bradycardia has occurred in long-term studies.

6.2 Postmarketing Experience

The following adverse reactions have been identified during post-approval use of trazodone hydrochloride tablets. Because these reactions are reported voluntarily from a population of uncertain size, it is not always possible to estimate their frequency or establish a causal relationship to drug exposure:

Blood and lymphatic system disorders:hemolytic anemia, leukocytosis

Cardiac disorders:cardiospasm, congestive heart failure, conduction block, orthostatic hypotension and syncope, palpitations, bradycardia, atrial fibrillation, myocardial infarction, cardiac arrest, arrhythmia, ventricular ectopic activity, including ventricular tachycardia and QT prolongation. Prolonged QT interval, torsade de pointes, and ventricular tachycardia have been reported at doses of 100 mg per day or less [see Warnings and Precautions (5.3)].

Endocrine disorders:inappropriate ADH syndrome

Eye disorders:diplopia

Gastrointestinal disorders:increased salivation, nausea/vomiting

General disorders and administration site conditions:chills, edema, unexplained death, weakness

Hepatobiliary disorders:cholestasis, jaundice, hyperbilirubinemia, liver enzyme alterations

Investigations:increased amylase

Metabolism and nutrition disorders:methemoglobinemia

Nervous system disorders:aphasia, ataxia, cerebrovascular accident, extrapyramidal symptoms, grand mal seizures, paresthesia, tardive dyskinesia, vertigo

Psychiatric disorders:abnormal dreams, agitation, anxiety, hallucinations, insomnia, paranoid reaction, psychosis, stupor

Renal and urinary disorders:urinary incontinence, urinary retention

Reproductive system and breast disorders:breast enlargement or engorgement, clitorism, lactation, priapism [see Warnings and Precautions (5.6)]

Respiratory, thoracic and mediastinal disorders:apnea

Skin and subcutaneous tissue disorders:alopecia, hirsutism, leukonychia, pruritus, psoriasis, rash, urticaria

Vascular disorders:vasodilation

7 DRUG INTERACTIONS

7.1 Drugs Having Clinically Important Interactions with Trazodone Hydrochloride Tablets

Table 3: Clinically Important Drug Interactions with Trazodone Hydrochloride Tablets
Monoamine Oxidase Inhibitors (MAOIs)
Clinical Impact: | The concomitant use of MAOIs and serotonergic drugs including trazodone hydrochloride tablets increases the risk of serotonin syndrome.
Intervention: | Trazodone hydrochloride tablets are contraindicated in patients taking MAOIs, including MAOIs such as linezolid or intravenous methylene blue [see Contraindications (4), Dosage and Administration (2.3, 2.4), and Warnings and Precautions (5.2)].
Examples: | isocarboxazid, moclobemide, phenelzine, selegiline, tranylcypromine
Other Serotonergic Drugs
Clinical Impact: | The concomitant use of serotonergic drugs including trazodone hydrochloride tablets and other serotonergic drugs increases the risk of serotonin syndrome.
Intervention: | Monitor patients for signs and symptoms of serotonin syndrome, particularly during trazodone hydrochloride tablets initiation. If serotonin syndrome occurs, consider discontinuation of trazodone hydrochloride tablets and/or concomitant serotonergic drugs [see Warnings and Precautions (5.2)].
Examples: | triptans, antidepressants (tricyclic and serotonin uptake inhibitors), fentanyl, lithium, tramadol, tryptophan, buspirone, and St. John's Wort
Antiplatelet Agents and Anticoagulants
Clinical Impact: | Serotonin release by platelets plays an important role in hemostasis. The concurrent use of an antiplatelet agent or anticoagulant with trazodone hydrochloride tablets may potentiate the risk of bleeding.
Intervention: | Inform patients of the increased risk of bleeding with the concomitant use of trazodone hydrochloride tablets and antiplatelet agents and anticoagulants. For patients taking warfarin, carefully monitor the international normalized ratio (INR) when initiating or discontinuing trazodone hydrochloride tablets [see Warnings and Precautions (5.5)].
Examples: | warfarin, rivaroxaban, dabigatran, clopidogrel
Strong CYP3A4 Inhibitors
Clinical Impact: | The concomitant use of trazodone hydrochloride tablets and strong CYP3A4 inhibitors increased the exposure of trazodone compared to the use of trazodone hydrochloride tablets alone.
Intervention: | If trazodone hydrochloride tablets is used with a potent CYP3A4 inhibitor, the risk of adverse reactions, including cardiac arrhythmias, may be increased and a lower dose of trazodone hydrochloride tablets should be considered [see Dosage and Administration (2.5), Warnings and Precautions (5.3)].
Examples: | itraconazole, ketoconazole, clarithromycin, indinavir
Strong CYP3A4 Inducers
Clinical Impact: | The concomitant use of trazodone hydrochloride tablets and strong CYP3A4 inducers decreased the exposure of trazodone compared to the use of trazodone hydrochloride tablets alone.
Intervention: | Patients should be closely monitored to see if there is a need for an increased dose of trazodone hydrochloride tablets when taking CYP3A4 inducers [see Dosage and Administration (2.5)].
Examples: | rifampin, carbamazepine, phenytoin, St. John’s wort
Digoxin and Phenytoin
Clinical Impact: | Digoxin and phenytoin are narrow therapeutic index drugs. Concomitant use of trazodone hydrochloride tablets can increase digoxin or phenytoin concentrations.
Intervention: | Measure serum digoxin or phenytoin concentrations before initiating concomitant use of trazodone hydrochloride tablets. Continue monitoring and reduce digoxin or phenytoin dose as necessary.
Examples: | digoxin, phenytoin
Central Nervous System (CNS) Depressants
Clinical Impact: | Trazodone hydrochloride tablets may enhance the response CNS depressants.
Intervention: | Patients should be counseled that trazodone hydrochloride tablets may enhance the response to alcohol, barbiturates, and other CNS depressants.
Examples: | alcohol, barbiturates
QT Interval Prolongation
Clinical Impact: | Concomitant use of drugs that prolong the QT interval may add to the QT effects of trazodone hydrochloride tablets and increase the risk of cardiac arrhythmia.
Intervention: | Avoid the use of trazodone hydrochloride tablets in combination with other drugs known to prolong QTc [see Warnings and Precautions (5.3)].
Examples: | Class 1A antiarrhythmics: quinidine, procainamide, disopyramide; Class 3 antiarrhythmics: amiodarone, sotalol; Antipsychotics: ziprasidone, chlorpromazine, thioridazine; Antibiotics: gatifloxacin

8 USE IN SPECIFIC POPULATIONS

8.1 Pregnancy

Pregnancy Exposure Registry

There is a pregnancy exposure registry that monitors pregnancy outcomes in women exposed to antidepressants during pregnancy. Healthcare providers are encouraged to register patients by calling the National Pregnancy Registry for Antidepressants at 1-844-405-6185 or visiting online at https://womensmentalhealth.org/clinical-and-research-programs/pregnancyregistry/antidepressants/

Risk Summary

Published prospective cohort studies, case series, and case reports over several decades with trazodone hydrochloride use in pregnant women have not identified any drug-associated risks of major birth defects, miscarriage, or adverse maternal or fetal outcomes (see Data). Trazodone hydrochloride has been shown to cause increased fetal resorption and other adverse effects on the fetus in the rat when given at dose levels approximately 7.3 to 11 times the maximum recommended human dose (MRHD) of 400 mg/day in adults on a mg/m^2basis. There was also an increase in congenital anomalies in the rabbit at approximately 7.3 to 22 times the MRHD on a mg/m^2basis (see Data).

The estimated background risk of major birth defects and miscarriage for the indicated population is unknown. All pregnancies have a background risk of birth defect, loss, or other adverse outcomes. In the U.S. general population, the estimated background risk of major birth defects and miscarriage in clinically recognized pregnancies is 2% to 4% and 15% to 20%, respectively.

Clinical Considerations

Disease-associated maternal and/or embryofetal risk

A prospective, longitudinal study followed 201 pregnant women with a history of major depressive disorder who were euthymic and taking antidepressants at the beginning of pregnancy. The women who discontinued antidepressants during pregnancy were more likely to experience a relapse of major depression that women who continued antidepressants. Consider the risk of untreated depression when discontinuing or changing treatment with antidepressant medication during pregnancy and postpartum.

Data

Human Data

While available studies cannot definitively establish the absence of risk, published data from prospective cohort studies, case series, and case reports over several decades have not identified an association with trazodone use during pregnancy and major birth defects, miscarriage, or other adverse maternal or fetal outcomes. All available studies have methodological limitations, including small sample size and inconsistent comparator groups.

Animal Data

No teratogenic effects were observed when trazodone was given to pregnant rats and rabbits during the period of organogenesis at oral doses up to 450 mg/kg/day. This dose is 11 and 22 times, in rats and rabbits, respectively, the maximum recommended human dose (MRHD) of 400 mg/day in adults on a mg/m^2basis. Increased fetal resorption and other adverse effects on the fetus in rats at 7.3 to 11 times the MRHD and increase in congenital anomalies in rabbits at 7.3 to 22 times the MRHD on a mg/m^2basis were observed. No further details on these studies are available.

8.2 Lactation

Risk Summary

Data from published literature report the transfer of trazodone into human milk. There are no data on the effect of trazodone on milk production. Limited data from postmarketing reports have not identified and association of adverse effects on the breastfed child. The developmental and health benefits of breastfeeding should be considered along with the mother’s clinical need for trazodone hydrochloride and any potential adverse effects on the breastfed child from trazodone hydrochloride or from the underlying maternal condition.

8.4 Pediatric Use

Safety and effectiveness in the pediatric population have not been established. Antidepressants increased the risk of suicidal thoughts and behaviors in pediatric patients [see Boxed Warning, Warnings and Precautions (5.1)] .

8.5 Geriatric Use

Reported clinical literature and experience with trazodone has not identified differences in responses between elderly and younger patients. However, as experience in the elderly with trazodone hydrochloride is limited, it should be used with caution in geriatric patients.

Serotonergic antidepressants have been associated with cases of clinically significant hyponatremia in elderly patients, who may be at greater risk for this adverse reaction [see Warnings and Precautions (5.11)].

8.6 Renal Impairment

Trazodone has not been studied in patients with renal impairment. Trazodone should be used with caution in this population.

8.7 Hepatic Impairment

Trazodone has not been studied in patients with hepatic impairment. Trazodone should be used with caution in this population.

9 DRUG ABUSE AND DEPENDENCE

9.1 Controlled Substance

Trazodone hydrochloride tablets are not a controlled substance.

9.2 Abuse

Although trazodone hydrochloride has not been systematically studied in preclinical or clinical studies for its potential for abuse, no indication of drug-seeking behavior was seen in the clinical studies with trazodone hydrochloride.

10 OVERDOSAGE

Death from overdose has occurred in patients ingesting trazodone hydrochloride and other CNS depressant drugs concurrently (alcohol; alcohol and chloral hydrate and diazepam; amobarbital; chlordiazepoxide; or meprobamate).

The most severe reactions reported to have occurred with overdose of trazodone hydrochloride alone have been priapism, respiratory arrest, seizures, ECG changes, including QT prolongation and syndrome of inappropriate antidiuretic hormone secretion (SIADH). The reactions reported most frequently have been drowsiness and vomiting. Overdosage may cause an increase in incidence or severity of any of the reported adverse reactions.

There is no specific antidote for trazodone hydrochloride overdose. In managing overdosage, consider the possibility of multiple drug involvement. For current information on the management of poisoning or overdose, contact a poison control center (1-800-222-1222 or www.poison.org).

11 DESCRIPTION

Trazodone hydrochloride tablets, USP for oral administration contain trazodone hydrochloride, USP a selective serotonin reuptake inhibitor and 5HT2 receptor antagonist. Trazodone hydrochloride, USP is a triazolopyridine derivative designated as 2-[3-[4-(3-chlorophenyl)-1-piperazinyl]propyl]-1,2,4-triazolo[4, 3-a]pyridin-3(2 H)-one hydrochloride. It is a white, odorless crystalline powder which is freely soluble in water. The structural formula is represented as follows:

C19H22CIN5O • HCl M.W. 408.32

Each tablet, for oral administration, contains 50 mg, 100 mg or 150 mg of trazodone hydrochloride, USP. In addition, each tablet contains colloidal silicon dioxide, lactose anhydrous, magnesium stearate, microcrystalline cellulose and sodium starch glycolate.

12 CLINICAL PHARMACOLOGY

12.1 Mechanism of Action

The mechanism of trazodone’s antidepressant action is not fully understood, but is thought to be related to its enhancement of serotonergic activity in the CNS. Trazodone is both a selective serotonin reuptake inhibitor (SSRI) and a 5HT2 receptor antagonist and the net result of this action on serotonergic transmission and its role in trazodone’s antidepressant effect is unknown.

12.2 Pharmacodynamics

Preclinical studies have shown that trazodone selectively inhibits neuronal reuptake of serotonin (Ki = 367 nM) and acts as an antagonist at 5-HT-2A (Ki = 35.6 nM) serotonin receptors. Trazodone is also an antagonist at several other monoaminergic receptors including 5-HT2B (Ki = 78.4 nM), 5-HT2C (Ki = 224 nM), α1A (Ki = 153 nM), α2C (Ki = 155 nM) receptors and it is a partial agonist at 5- HT1A (Ki = 118 nM) receptor.

Trazodone antagonizes alpha 1-adrenergic receptors, a property which may be associated with postural hypotension.

12.3 Pharmacokinetics

Absorption

In humans, trazodone hydrochloride is absorbed after oral administration without selective localization in any tissue. When trazodone hydrochloride is taken shortly after ingestion of food, there may be an increase in the amount of drug absorbed, a decrease in maximum concentration and a lengthening in the time to maximum concentration. Peak plasma levels occur approximately one hour after dosing when trazodone hydrochloride is taken on an empty stomach or 2 hours after dosing when taken with food.

Metabolism

In vitrostudies in human liver microsomes show that trazodone is metabolized, via oxidative cleavage, to an active metabolite, m-chlorophenylpiperazine (mCPP) by CYP3A4. Other metabolic pathways that may be involved in the metabolism of trazodone have not been well characterized. Trazodone is extensively metabolized; less than 1% of an oral dose is excreted unchanged in the urine.

Elimination

In some patients trazodone may accumulate in the plasma.

Protein Binding

Trazodone is 89 to 95% protein bound in vitroat concentrations attained with therapeutic doses in humans.

13 NONCLINICAL TOXICOLOGY

13.1 Carcinogenesis, Mutagenesis, Impairment of Fertility

Carcinogenesis

No drug- or dose-related occurrence of carcinogenesis was evident in rats receiving trazodone in daily oral doses up to 7.3 times the maximum recommended human dose (MRHD) of 400 mg/day in adults on a mg/m^2basis.

Mutagenesis

No genotoxicity studies were conducted with trazodone.

Impairment of Fertility

Trazodone has no effect on fertility in rats at doses up to 7.3 times the MRHD in adults on a mg/m^2basis.

14 CLINICAL STUDIES

The efficacy and safety of trazodone hydrochloride were established from inpatient and outpatient trials of the trazodone immediate release formulation in the treatment of major depressive disorder.

16 HOW SUPPLIED/STORAGE AND HANDLING

Trazodone hydrochloride tablets, USP are available as follows:

100 mg: White, round, compressed tablet, debossed “PLIVA 434” on one side and scored on the other side. Available in bottles of :

30 tablet NDC 72789-424-30

90 tablet NDC 72789-424-90

Directions for using the correct score when breaking the tablet please refer to the following:

-For 50 mg, break the score on either the left or right side of the tablet (one-third of a tablet).

-For 75 mg, break the score down the middle of the tablet (one-half of a tablet).

-For 100 mg, break the score on either the left or right side of the tablet (two-thirds of a tablet).

-For 150 mg, use the entire tablet.

Store at 20° to 25°C (68° to 77°F); excursions permitted to 15° to 30°C (59° to 86°F) [see USP Controlled Room Temperature].

Dispense in a tight, light-resistant container as defined in the USP.

Keep this and all medications out of the reach of children.

17 PATIENT COUNSELING INFORMATION

Advise the patient to read the FDA-approved patient labeling (Medication Guide).

Suicidal Thoughts and Behaviors

Advise patients and caregivers to look for the emergence of suicidality, especially early during treatment and when the dosage is adjusted up or down and instruct them to report such symptoms to the healthcare provider [see Box Warning and Warnings and Precautions (5.1)].

Dosage and Administration

Advise patients that trazodone hydrochloride tablets should be taken shortly after a meal or light snack. Advise patients regarding the importance of following dosage titration instructions [see Dosage and Administration (2)].

Serotonin Syndrome

Caution patients about the risk of serotonin syndrome, particularly with the concomitant use of trazodone hydrochloride tablets with other serotonergic drugs including triptans, tricyclic antidepressants, fentanyl, lithium, tramadol, tryptophan, buspirone, St. John’s Wort, and with drugs that impair metabolism of serotonin (in particular, MAOIs, both those intended to treat psychiatric disorders and also others, such as linezolid). Patients should contact their health care provider or report to the emergency room if they experience signs or symptoms of serotonin syndrome [see Warnings and Precautions (5.2) and Drug Interactions (7)].

Activation of Mania/Hypomania

Advise patients and their caregivers to observe for signs of activation of mania/hypomania and instruct them to report such symptoms to the healthcare provider [see Warnings and Precautions (5.7)] .

Increased Risk of Bleeding

Inform patients about the concomitant use of trazodone hydrochloride tablets with aspirin, NSAIDs, other antiplatelet drugs, warfarin, or other anticoagulants because the combined use of drugs that interfere with serotonin reuptake and these medications has been associated with an increased risk of bleeding. Advise them to inform their health care providers if they are taking or planning to take any prescription or over-the-counter medications that increase the risk of bleeding [see Warnings and Precautions (5.5)].

Discontinuation Syndrome

Advise patients not to abruptly discontinue trazodone hydrochloride tablets and to discuss any tapering regimen with their healthcare provider. Adverse reactions can occur when trazodone hydrochloride tablets is discontinued [see Warnings and Precautions (5.8)].

Concomitant Medications

Advise patients to inform their health care providers if they are taking, or plan to take any prescription or over-the-counter medications since there is a potential for interactions [see Drug Interactions (7.1)].

Pregnancy

Advise patients to notify their healthcare provider if they become pregnant or intend to become pregnant during therapy with trazodone hydrochloride tablets. Advise patients that there is a pregnancy exposure registry that monitors pregnancy outcomes in women exposed to trazodone hydrochloride tablets during pregnancy [see Use in Special Populations (8.1)].

Manufactured In Croatia By:
Pliva Hrvatska d.o.o.
Zagreb, Croatia

Manufactured For:
Teva Pharmaceuticals
Parsippany, NJ 07054

Rev. L 7/2025

MEDICATION GUIDE

Trazodone Hydrochloride (traz' oh done hye'' droe klor' ide) Tablets

for oral use

What is the most important information I should know about trazodone hydrochloride tablets?

Antidepressant medicines, depression or other serious mental illnesses, and suicidal thoughts or actions: Talk to your healthcare provider about:

- All risks and benefits of treatment with antidepressant medicines

- All treatment choices for depression or other serious mental illnesses

1. Antidepressant medicines may increase suicidal thoughts or actions in some children, teenagers, and young adults within the first few months of treatment.
2. Depression and other serious mental illnesses are the most important causes of suicidal thoughts and actions. Some people may have a higher risk of having suicidal thoughts or actions. These include people who have or have a family history of bipolar illness (also called manic-depressive illness) or suicidal thoughts or actions.
3. How can I watch for and try to prevent suicidal thoughts and actions?

- Pay close attention to any changes, especially sudden changes in mood, behaviors, thoughts, or feelings. This is very important when an antidepressant medicine is started or when the dose is changed.
- Call your healthcare provider right away to report new or sudden changes in mood, behavior, thoughts or feelings.
- Keep all follow-up visits with your healthcare provider as scheduled. Call your healthcare provider between visits as needed, especially if you are worried about symptoms.

Call a healthcare provider right away if you have any of the following symptoms, especially if they are new, worse, or worry you:

- Thoughts about suicide or dying
- Attempts to commit suicide
- New or worse depression
- New or worse anxiety
- Feeling very agitated or restless
- Panic attacks
- Trouble sleeping (insomnia)
- New or worse irritability
- Acting aggressive, being angry or violent
- Acting on dangerous impulses
- An extreme increase in activity and talking (mania)

- Other unusual changes in behavior or mood

What else do I need to know about antidepressant medicines?

- Never stop an antidepressant medicine without first talking to a healthcare provider.Stopping an antidepressant medicine suddenly can cause other symptoms.
- Antidepressants are medicines used to treat depression and other illnesses.It is important to discuss all the risks of treating depression and also the risks of not treating it. You should discuss all treatment choices with your healthcare provider, not just the use of antidepressants.
- Antidepressant medicines have other side effects.Talk to your healthcare provider about the side effects of your medicines.

- Antidepressant medicines can interact with other medicines.Know all of the medicines that you take. Keep a list of all medicines to show your healthcare provider. Do not start new medicines without first checking with your healthcare provider.

It is not known if trazodone hydrochloride tablets are safe and effective in children.

What are trazodone hydrochloride tablets?Trazodone hydrochloride tablets are a prescription medicine used in adults to treat major depressive disorder (MDD). Trazodone hydrochloride tablets belong to a class of medicines known as SSRIs (or selective serotonin reuptake inhibitors).

Do not take trazodone hydrochloride tablets:

- If you take a monoamine oxidase inhibitor (MAOI). Ask your healthcare provider or pharmacist if you are not sure if you take an MAOI, including the antibiotic linezolid, and intravenous methylene blue.

- Do not take an MAOI within 2 weeks of stopping trazodone hydrochloride tablets unless directed to do so by your healthcare provider.

- Do not start trazodone hydrochloride tablets if you stopped taking an MAOI in the last 2 weeks unless directed to do so by your healthcare provider.

Before you take trazodone hydrochloride tablets tell your healthcare provider about all of your medical conditions, including if you:

- have heart problems, including QT prolongation or a family history of it
- have ever had a heart attack
- have bipolar disorder
- have liver or kidney problems
- have other serious medical conditions
- are pregnant or plan to become pregnant. It is not known if trazodone hydrochloride tablets will harm your unborn baby. Talk to your healthcare provider about the risk to your unborn baby if you take trazodone hydrochloride tablets.
  - If you become pregnant during treatment with trazodone hydrochloride tablets, talk to your healthcare provider about registering with the National Pregnancy Registry for Antidepressants. You can register by calling 1-844-405-6185.
- are breastfeeding or plan to breastfeed. Trazodone hydrochloride passes into your breast milk. Talk to your healthcare provider about the best way to feed your baby if you take trazodone hydrochloride.
- have taken a Monoamine Oxidase Inhibitor (MAOI) or if you have stopped taking an MAOI in the last 2 weeks.
  Tell your healthcare provider about all the medicines you take,including prescription and over-the-counter medicines, vitamins, and herbal supplements. Using trazodone hydrochloride tablets with certain other medicines can affect each other causing serious side effects.
  Especially tell your healthcare provider if you take:
- triptans used to treat migraine headache
- medicines used to treat mood, anxiety, psychotic or thought disorders, including tricyclics, lithium, SSRIs, SNRIs, buspirone, or antipsychotics
- tramadol
- over-the-counter supplements such as tryptophan or St. John’s Wort
- nonsteroidal anti-inflammatory drugs (NSAIDS)
- aspirin
- warfarin (Coumadin, Jantoven)
- phenytoin (Mesantoin)
- diuretics

Know the medicines you take. Keep a list of them and show it to your healthcare provider and pharmacist when you get a new medicine.

How should I take trazodone hydrochloride tablets?

- Take trazodone hydrochloride tablets exactly as your healthcare provider tells you.
- Trazodone hydrochloride tablets should be taken shortly after a meal or light snack.
- If you feel drowsy after taking trazodone hydrochloride tablets, talk to your healthcare provider. Your healthcare provider may change your dose or the time of day you take your trazodone hydrochloride tablets.
- Do not stop taking trazodone hydrochloride tablets without talking to your healthcare provider.
- Trazodone hydrochloride tablets should be swallowed whole or broken in half along the score line. Do not chew or crush trazodone hydrochloride tablets. Tell your healthcare provider if you cannot swallow trazodone either whole or as a half tablet.

- If you take too many trazodone hydrochloride tablets, call your healthcare provider, your Poison Control Center at 1-800-222-1222, or go to the nearest emergency room right away.

What should I avoid while taking trazodone hydrochloride tablets?

- Do not drive, operate heavy machinery, or do other dangerous activities until you know how trazodone hydrochloride tablets affects you. Trazodone hydrochloride tablets can slow your thinking and motor skills.

- Do not drink alcohol or take other medicines that make you sleepy or dizzy while taking trazodone hydrochloride tablets until you talk with your healthcare provider. Trazodone hydrochloride tablets may make your sleepiness or dizziness worse if you take it with alcohol or other medicines that cause sleepiness or dizziness.

What are the possible side effects of trazodone hydrochloride tablets?

Trazodone hydrochloride tablets can cause serious side effects or death, including:

- See “What is the most important information I should know about trazodone hydrochloride tablets?”
- Serotonin syndrome.Symptoms of serotonin syndrome include: agitation, hallucinations, problems with coordination, fast heartbeat, tight muscles, trouble walking, sweating, fever, nausea, vomiting, and diarrhea.
- Irregular or fast heartbeat or faint (QT prolongation)
- Low blood pressure.You feel dizzy or faint when you change positions (go from sitting to standing)
- Unusual bruising or bleeding
- Erection lasting for more than 6 hours (priapism)
- Feeling high or in a very good mood, then becoming irritable, or having too much energy, feeling like you have to keep talking or do not sleep (mania).
- Withdrawal symptoms.Symptoms of withdrawal can include anxiety, agitation, and sleep problems. Do not stop taking trazodone hydrochloride tablets without talking to your healthcare provider.
- Visualproblems.
  - eye pain
  - changes in vision
  - swelling or redness in or around the eye

Only some people are at risk for these problems. You may want to undergo an eye examination to see if you are at risk and receive preventative treatment if you are.

- Low sodium in your blood (hyponatremia).Symptoms of hyponatremia include: headache, feeling weak, feeling confused, trouble concentrating, memory problems and feeling unsteady when you walk.

Get medical help right away, if you have any of the symptoms listed above.

The most common side effects of trazodone hydrochloride tablets include:

- swelling
- blurred vision

- dizziness

- sleepiness

- tiredness

- diarrhea

- stuffy nose

- weight loss

These are not all the possible side effects of trazodone hydrochloride tablets. Call your doctor for medical advice about side effects. You may report side effects to FDA at 1-800-FDA-1088.

How should I store trazodone hydrochloride tablets?

- Store trazodone hydrochloride tablets at room temperature between 68°F to 77°F (20°C to 25°C).
- Keep in tight container
- Keep out of the light
- Safely throw away medicine that is out of date or no longer needed.

Keep trazodone hydrochloride tablets and all medicines out of the reach of children.

General information about the safe and effective use of trazodone hydrochloride tablets.

Medicines are sometimes prescribed for purposes other than those listed in a Medication Guide. Do not use trazodone hydrochloride tablets for a condition for which it was not prescribed. Do not give trazodone hydrochloride tablets to other people, even if they have the same symptoms that you have. It may harm them. You can ask your pharmacist or healthcare provider for information about trazodone hydrochloride tablets that is written for health professionals.

What are the ingredients in trazodone hydrochloride tablets?

Active ingredient:trazodone hydrochloride, USP

Inactive ingredients:colloidal silicon dioxide, lactose anhydrous, magnesium stearate, microcrystalline cellulose and sodium starch glycolate.

Brands listed are trademarks of their respective owners.

Manufactured In Croatia By: Pliva Hrvatska d.o.o.,Zagreb, Croatia

Manufactured For: Teva Pharmaceuticals,Parsippany, NJ 07054

This Medication Guide has been approved by the U.S. Food and Drug Administration Rev. G 7/2025

Package/Label Display Panel

traZODone Hydrochloride Tablets, USP

100 mg

PHARMACIST: Dispense the accompanying Medication Guide to each patient.

Rx only